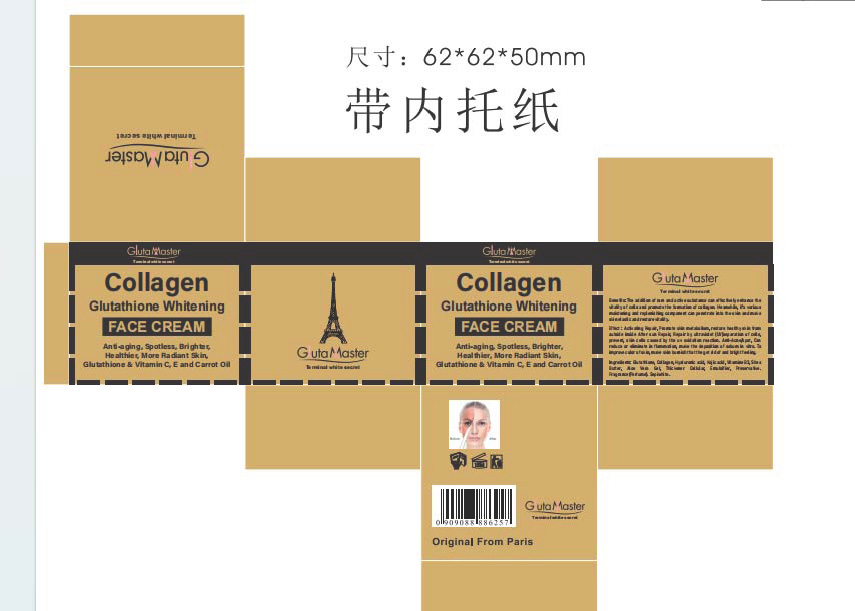 DRUG LABEL: Collagen Glutathione Whitening FACECREAM
NDC: 84423-054 | Form: CREAM, AUGMENTED
Manufacturer: Guangzhou Kadiya Biotechnology Co., Ltd.
Category: otc | Type: HUMAN OTC DRUG LABEL
Date: 20241004

ACTIVE INGREDIENTS: ALOE VERA LEAF 1.5 g/50 g; ALPHA-ARBUTIN 0.5 g/50 g; GLUTATHIONE 0.05 g/50 g
INACTIVE INGREDIENTS: PHENOXYETHANOL; TITANIUM DIOXIDE; ALLANTOIN; TROLAMINE; PEG-75 LANOLIN; WATER; GLYCERIN; HYDROXYACETOPHENONE; BUTYLENE GLYCOL; STEARYL ALCOHOL; STEARIC ACID; PORTULACA OLERACEA WHOLE; CETYL ALCOHOL; MYRISTIC ACID; LAURIC ACID; DIMETHICONE; FD&C YELLOW NO. 6; PALMITIC ACID; POLYSORBATE 60; PELARGONIUM GRAVEOLENS WHOLE; MINERAL OIL; CHAMAEMELUM NOBILE FLOWER; CHAMAEMELUM NOBILE WHOLE; 1,2-HEXANEDIOL; TRANEXAMIC ACID; GLYCERYL MONOSTEARATE; METHYLPARABEN; FD&C YELLOW NO. 5; SODIUM CHLORIDE; ALUMINUM OXIDE

PURPOSE

For facial skin cleansing, exfoliation and whitening moisturization

INACTIVE INGREDIENT

AQUA，GLYCERIN，MINERAL OIL，BIFIDA FERMENT FILTRATE，HYDROXYACETOPHENONE，1,2-HEXANEDIOL，BUTYLENE GLYCOL，PALMITIC ACID，STEARIC ACID，MYRISTIC ACID，LAURIC ACID，DIMETHICONE，GLYCERYL STEARATE，POLYSORBATE 60，BUTYLENE GLYCOL，ALOE BARBADENSIS LEAF EXTRACT，STEARYL ALCOHOL，CETYL ALCOHOL，TRANEXAMIC ACID，TITANIUM DIOXIDE，ALUMINA，HYDROGENATED LECITHIN，TRIETHANOLAMINE，PEG-75 LANOLIN，PHENOXYETHANOL，ALLANTOIN，METHYLPARABEN，FRAGRANCE，CI 19140，SODIUM CHLORIDE，CI 15985

WARNINGS

1、For external use only, avoid contact with eyes when used
2、Keep out of reach of children

INDICATIONS AND USAGE

For facial skin cleansing, exfoliation and whitening moisturization

DOSAGE AND ADMINISTRATION

Once in the morning and once in the evening

KEEP OUT OF REACH OF CHILDREN SECTION

Active Ingredients
Glutathione0.1%
ALPHA-ARBUTIN1%
HYDROLYZED COLLAGEN EXTRACT3%
ALOE BARBADENSIS LEAF EXTRACT3%

PACKAGE LABEL

Active Ingredients
Glutathione0.1%
ALPHA-ARBUTIN1%
HYDROLYZED COLLAGEN EXTRACT3%
ALOE BARBADENSIS LEAF EXTRACT3%

Uses：
For facial skin cleansing, exfoliation and whitening moisturization
The storage method：
Store sealed in a cool place and out of sunlight

Warning.
1、For external use only, avoid contact with eyes when used
2、Keep out of reach of children

Inactive ingredients：
AQUA，GLYCERIN，MINERAL OIL，BIFIDA FERMENT FILTRATE，HYDROXYACETOPHENONE，1,2-HEXANEDIOL，BUTYLENE GLYCOL，PALMITIC ACID，STEARIC ACID，MYRISTIC ACID，LAURIC ACID，DIMETHICONE，GLYCERYL STEARATE，POLYSORBATE 60，BUTYLENE GLYCOL，ALOE BARBADENSIS LEAF EXTRACT，STEARYL ALCOHOL，CETYL ALCOHOL，TRANEXAMIC ACID，TITANIUM DIOXIDE，ALUMINA，HYDROGENATED LECITHIN，TRIETHANOLAMINE，PEG-75 LANOLIN，PHENOXYETHANOL，ALLANTOIN，METHYLPARABEN，FRAGRANCE，CI 19140，SODIUM CHLORIDE，CI 15985